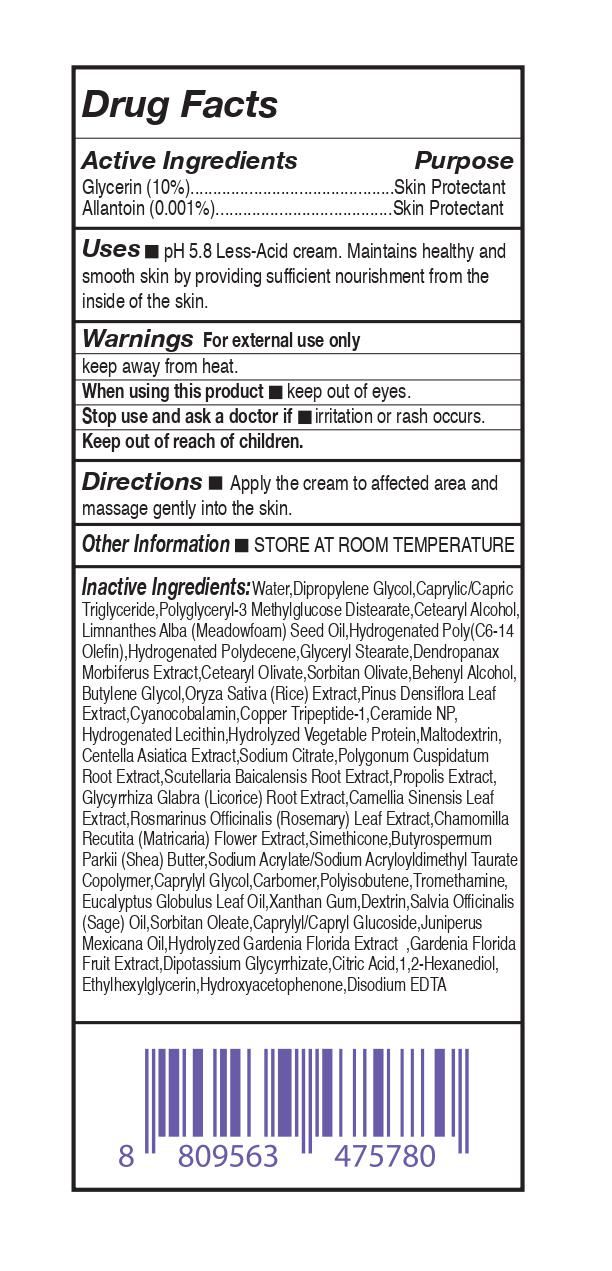 DRUG LABEL: repuera DermAtozyme 5% Ultra Moisture Cream
NDC: 81459-302 | Form: CREAM
Manufacturer: ALLUV
Category: otc | Type: HUMAN OTC DRUG LABEL
Date: 20210128

ACTIVE INGREDIENTS: ALLANTOIN 0.001 mg/100 mL; GLYCERIN 10 mg/100 mL
INACTIVE INGREDIENTS: DOCOSANOL; BUTYLENE GLYCOL; RICE GERM; PINUS DENSIFLORA LEAF; HYDROGENATED SOYBEAN LECITHIN; CHAMOMILE; CARBOMER HOMOPOLYMER, UNSPECIFIED TYPE; XANTHAN GUM; SAGE OIL; ETHYLHEXYLGLYCERIN; HYDROGENATED POLY(C6-14 OLEFIN; 2 CST); HYDROGENATED POLYDECENE (1500 CST); DIMETHICONE; POLYISOBUTYLENE (1000 MW); ICODEXTRIN; MEDIUM-CHAIN TRIGLYCERIDES; SORBITAN OLIVATE; CERAMIDE NP; POLYGLYCERYL-3 METHYLGLUCOSE DISTEARATE; SODIUM ACRYLATE/SODIUM ACRYLOYLDIMETHYLTAURATE COPOLYMER (4000000 MW); JUNIPERUS DEPPEANA WOOD OIL; GLYCYRRHIZINATE DIPOTASSIUM; EDETATE DISODIUM ANHYDROUS; CAPRYLYL/CAPRYL OLIGOGLUCOSIDE; WATER; DIPROPYLENE GLYCOL; CETOSTEARYL ALCOHOL; MEADOWFOAM SEED OIL; CETEARYL OLIVATE; GREEN TEA LEAF; ROSEMARY; CAPRYLYL GLYCOL; TROMETHAMINE; EUCALYPTUS OIL; SORBITAN MONOOLEATE; GARDENIA JASMINOIDES FRUIT; CITRIC ACID MONOHYDRATE; 1,2-HEXANEDIOL; HYDROXYACETOPHENONE; GLYCERYL MONOSTEARATE; CYANOCOBALAMIN; PREZATIDE COPPER; MALTODEXTRIN; CENTELLA ASIATICA; SODIUM CITRATE; POLYGONUM CUSPIDATUM ROOT; SCUTELLARIA BAICALENSIS ROOT; PROPOLIS WAX; GLYCYRRHIZA GLABRA; SHEA BUTTER

81459-302 re'puera DermAtozyme 5% Ultra Moisture Cream

Active Ingridients

Glycerin (10%)

Allantoin (0.001%)

Purpose

Skin Protectant

Uses

pH 5.8 Less-Acid cream. Maintains healthy and smooth skin by providing sufficient nourishment from the inside of the skin.

Warnings

For external use only

keep away from heat.

When using this product

keep out of eyes.

Stop use and ask a doctor if

irritation or rash occurs.

Keep out of reach of children.

Directions

Apply the cream to affected area and
massage gently into the skin.

Other Information

STORE AT ROOM TEMPERATURE

Inactive Ingredients

Water,Eucalyptus Globulus Leaf Oil, Dipropylene Glycol,Caprylic/Capric
Triglyceride,Polyglyceryl-3 Methylglucose Distearate,Cetearyl
Alcohol,Limnanthes Alba (Meadowfoam) Seed Oil,Hydrogenated
Poly(C6-14 Olefin),Hydrogenated Polydecene,Glyceryl Stearate,
Dendropanax Morbiferus Extract,Cetearyl Olivate,Sorbitan Olivate,
Behenyl Alcohol,Butylene Glycol,Oryza Sativa (Rice) Extract,Pinus
Densiflora Leaf Extract,Cyanocobalamin,Copper Tripeptide-1,
Ceramide NP,Hydrogenated Lecithin,Hydrolyzed Vegetable Protein,
Maltodextrin,Centella Asiatica Extract,Sodium Citrate,Polygonum
Cuspidatum Root Extract,Scutellaria Baicalensis Root Extract,
Propolis Extract,Glycyrrhiza Glabra (Licorice) Root Extract,Camellia
Sinensis Leaf Extract,Rosmarinus Officinalis(Rosemary) Leaf Extract,
Chamomilla Recutita (Matricaria) Flower Extract,Simethicone,
Butyrospermum Parkii (Shea) Butter,Sodium Acrylate/Sodium
Acryloyldimethyl Taurate Copolymer,Caprylyl Glycol,Carbomer,
Polyisobutene,Tromethamine,Xanthan Gum,Dextrin,Salvia Officinalis
(Sage) Oil,Sorbitan Oleate,Caprylyl/Capryl Glucoside,Juniperus
Mexicana Oil,Hydrolyzed Gardenia Florida Extract ,Gardenia Florida
Fruit Extract,Dipotassium Glycyrrhizate,Citric Acid,1,2-Hexanediol,
Ethylhexylglycerin,Hydroxyacetophenone,Disodium EDTA